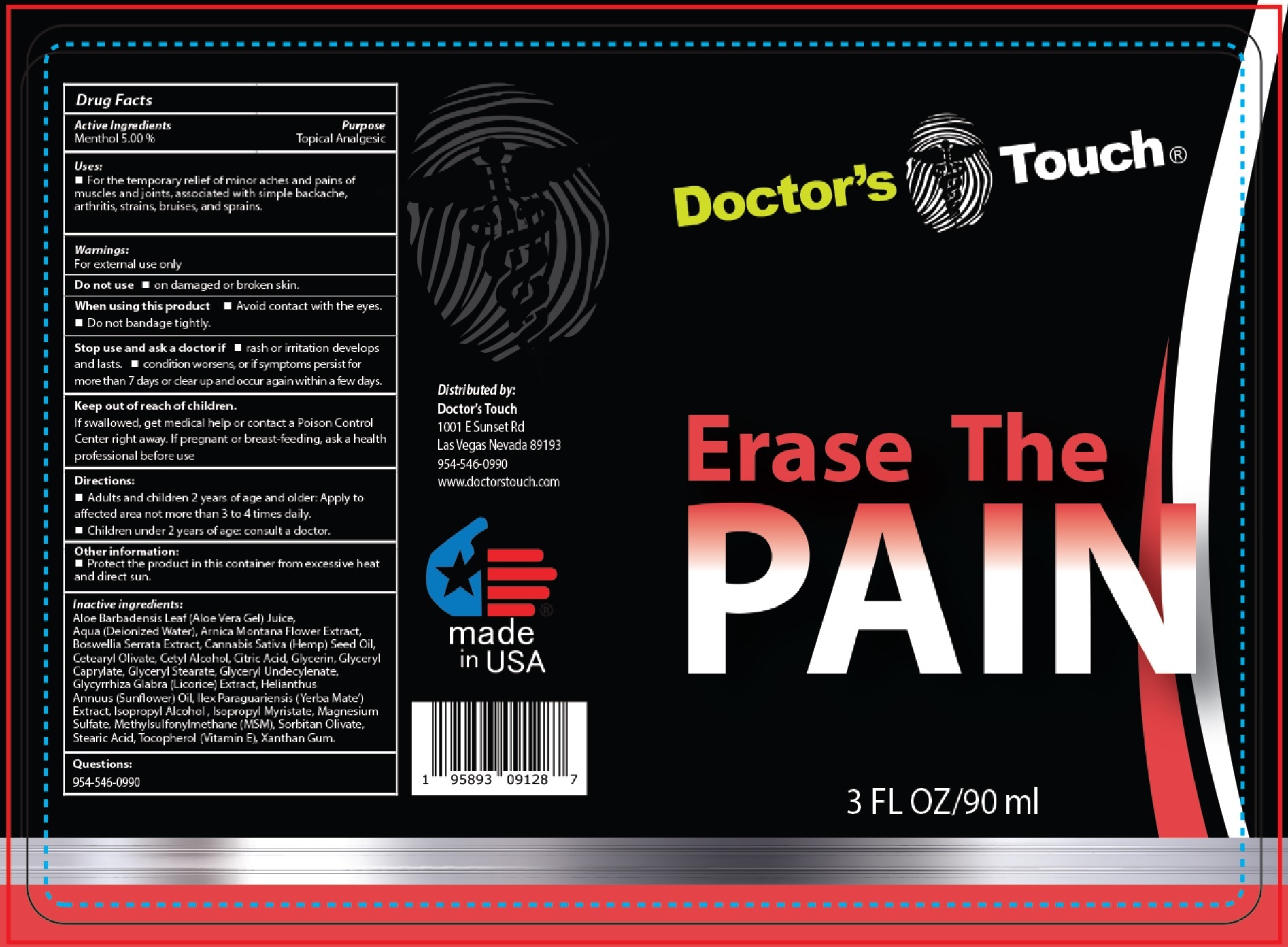 DRUG LABEL: DOCTORS TOUCH Erase The Pain
NDC: 80045-396 | Form: LIQUID
Manufacturer: DOCTOR'S CHOICE MEDICAL, LLC
Category: otc | Type: HUMAN OTC DRUG LABEL
Date: 20231106

ACTIVE INGREDIENTS: MENTHOL 50 mg/1 mL
INACTIVE INGREDIENTS: ALOE VERA LEAF; WATER; ARNICA MONTANA FLOWER; INDIAN FRANKINCENSE; CANNABIS SATIVA SEED OIL; CETEARYL OLIVATE; CETYL ALCOHOL; CITRIC ACID MONOHYDRATE; GLYCERIN; GLYCERYL MONOCAPRYLATE; GLYCERYL MONOSTEARATE; GLYCYRRHIZA GLABRA; HELIANTHUS ANNUUS FLOWERING TOP; ILEX PARAGUARIENSIS LEAF; ISOPROPYL ALCOHOL; ISOPROPYL MYRISTATE; MAGNESIUM SULFATE, UNSPECIFIED FORM; DIMETHYL SULFONE; SORBITAN OLIVATE; STEARIC ACID; TOCOPHEROL; XANTHAN GUM

DOCTOR'S TOUCH Erase The Pain

Active Ingredients

Menthol 5.00%

Purpose

Topical Analgesic

Uses:

- For the temporary relief of minor aches and pains of muscles and joints, associated with simple backache, arthritis, strains, bruises, and sprains.

Warnings:

For external use only

Do not use

- on damaged or broken skin

When using this product

- Avoid contact with the eyes.
- Do not bandage tightly.

Stop use and ask a doctor if

- rash or irritation develops and lasts.
- condition worsens, or if symptoms persist for more than 7 days or clear up and occur again within a few days.

Keep out of reach of children.

If swallowed, get medical help or contact a Poison Control Center right away.

If pregnant or breast-feeding,

ask a health professional before use

Directions:

- Adults and children 2 years of age and older: Apply to affected area not more than 3 to 4 times daily.
- Children under 2 years of age: consult a doctor.

Other information:

- Protect the product in this container from excessive heat and direct sun.

Inactive ingredients:

Aloe Barbadensis Leaf (Aloe Vera Gel) Juice, Aqua (Deionized Water), Arnica Montana Flower Extract, Boswellia Serrata Extract, Cannabis Sativa (Hemp) Seed Oil, Cetearyl Olivate, Cetyl Alcohol, Citric Acid, Glycerin, Glyceryl Caprylate, Glyceryl Stearate, Glyceryl Undecylenate, Glycyrrhiza Glabra (Licorice) Extract, Helianthus Annuus (Sunflower) Oil, Ilex Paraguariensis (Yerba Mate') Extract, Isopropyl Alcohol, Isopropyl Myristate, Magnesium Sulfate, Methylsulfonylmethane (MSM), Sorbitan Olivate, Stearic Acid, Tocopherol (Vitamin E), Xanthan Gum.

Questions:

954-546-0990